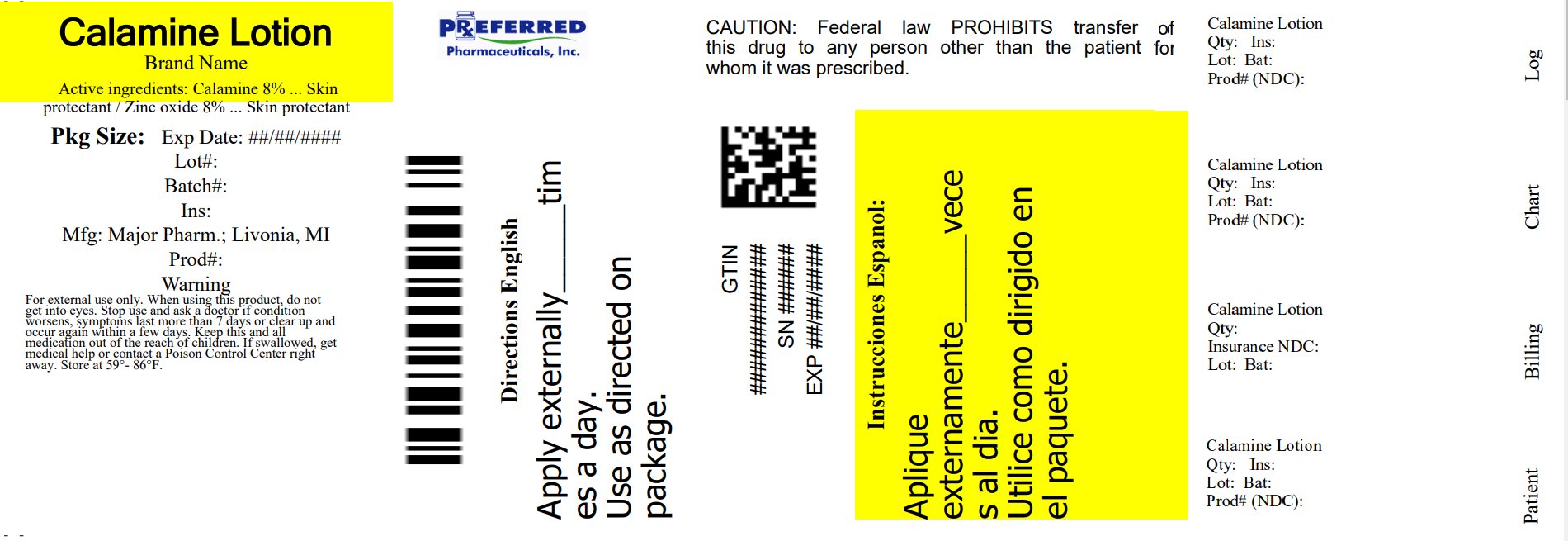 DRUG LABEL: Calamine
NDC: 68788-0292 | Form: LOTION
Manufacturer: Preferred Pharmaceuticals Inc.
Category: otc | Type: HUMAN OTC DRUG LABEL
Date: 20250212

ACTIVE INGREDIENTS: FERRIC OXIDE RED 8 g/1 mL; ZINC OXIDE 8 mg/1 mL
INACTIVE INGREDIENTS: BENTONITE; CALCIUM HYDROXIDE; GLYCERIN; WATER

Major 063.001 063AA

Active ingredents

Calamine 8%
Zinc oxide 8%

Purpose

Skin Protectant

Use

dries the oozing and weeping of poison:•ivy • oak • sumac

Warnings

For external use only

When using this product

Do not get into eyes

Stop use and ask a doctor if

- condition worsens
- symptoms last more than 7 days or clear up and occur again within a few days

Keep out of reach of children

If swallowed, get medical help or contact a Poison Control Center right away

Directions

- shake well before using
- apply as needed

Other information

store at 59⁰ - 86⁰ F

Inactive ingredients

bentonite magma, calcium hydroxide, glycerin, purified water

Questions or comments?

(800) 616-2471

Adverse reactions

Distributed By:

MAJOR PHARMACEUTICALS

17177 N LAUREL PARK DRIVE, SUITE 233

Livonia, MI 48152

Re-Order No 014282 M-97

Rev. 10/16

Relabeled By: Preferred Pharmaceuticals Inc.

principal display panel

NDC 68788-0292-1

MAJOR

Calamine

Lotion

Calamine Topical Suspension USP

Skin Protectant

Poison Ivy, Oak, Sumac

Drying Lotion

Shake well before using

6 FL OZ (177 mL)